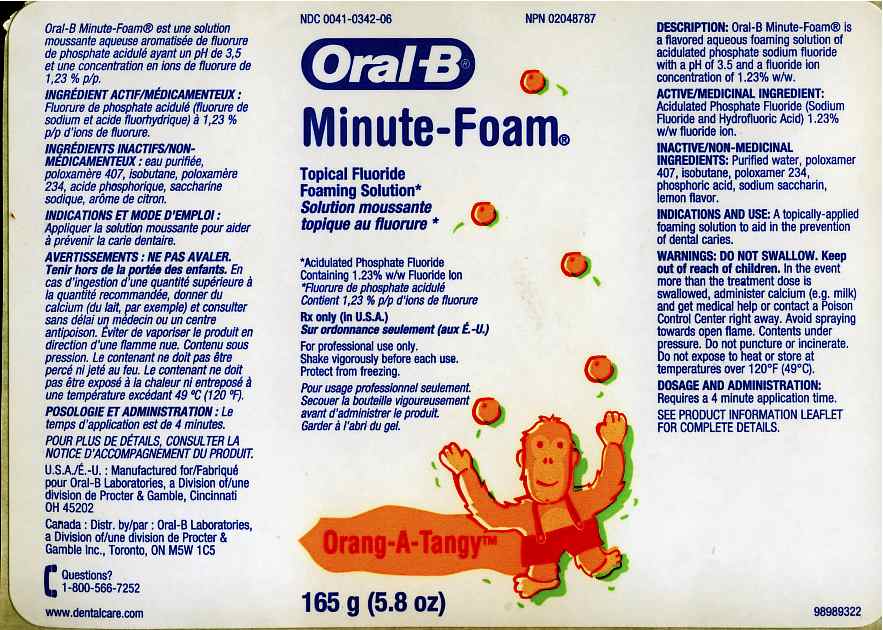 DRUG LABEL: Oral-B Minute-Foam Orang-A-Tangy
NDC: 0041-0342 | Form: AEROSOL
Manufacturer: Oral-B Laboratories
Category: prescription | Type: HUMAN PRESCRIPTION DRUG LABEL
Date: 20100927

ACTIVE INGREDIENTS: Sodium Fluoride 10 mg/1 g; Hydrofluoric Acid 2.3 mg/1 g

Package.Label Principal Display Panel

PATIENT INFORMATION

MINUTE-FOAM
Topical Fluoride Foaming Solution
(Acidulated Phosphate Fluoride Containing 1.23 % w/w Fluoride Ion)
FOR PROFESSIONAL USE ONLY
Active Ingredient: Acidulated Phosphate Fluoride (Sodium Fluoride and Hydrofluoric Acid) 1.23 % w/w fluoride ion.

DESCRIPTION

DESCRIPTION: Oral-B Minute Foam is a flavored aqueous foaming solution of acidulated phosphate sodium fluoride with pH of 3.5 and a fluoride ion concentration of 1.23% w/w.

INACTIVE INGREDIENT

Inactive Ingredients: Purified water, poloxamer 407, isobutane, poloxamer 234, phosphoric acid, sodium saccharin, flavor.

CLINICAL PHARMACOLOGY

CLINICAL PHARMACOLOGY: Acidulated Phosphate Fluoride inhibits caries formation by reducing enamel solubility and enhancing remineralization.

INDICATIONS AND USAGE

INDICATION AND USE: A topically-applied foaming solution to aid in the prevention of dental caries.

CONTRAINDICATIONS

CONTRAINDICATIONS: Do not use in patients with hypersensitivity to fluoride.
Do not use in patients with dysphagia.

WARNINGS: DO NOT SWALLOW
Accidental ingestion of the usual treatment dose (approx 12.4 mg of fluoride) is not harmful. In the event more than the treatment dose is swallowed, administer calcium (e.g. milk) and get medical or contact a Poison control Center right away. One bottle of Minute Foam contained 1.95 grams of fluoride ion which could be lethal for children adults.
Keep out of the reach of infants and children under 12 years.
Pediatric patients under age 12 should be supervised during use of this product.
Avoid spraying towards open flame.
Contents under pressure. Do not puncture or incinerate. Do not expose to heat or store at temperatures over 120 F (49 C).
PRECAUTIONS: FOR PROFESSIONAL USE ONLY
Laboratory studies have indicated that repeated use of Acidulated Phosphate Fluoride products may dull porcelain and composite restorations.
Safety and effectiveness below age 6 have not been established. There have been no long term studies with this product to evaluate carcinogenic, mutagenic or impairment of fertility potential.

Carcinogenesis, Mutagenesis, Impairment of Fertility:
No evidence of carcinogenicity was observed in female and male mice at doses ranging from 2.4 to 18.8 mg/kg sodium fluoride of body weight (3,4). Equivocal evidence of carcinogenicity was reported in male rats at doses ranging from 2.5 to 4.1 mg/kg fluoride, but no evidence of carcinogenicity was observed in female rates (3,4). In another study, no carcinogenicity was observed in rats treated with fluoride up to25 mg/kg of body weight (5). Overall, epidemiological studies do not show an association between fluoridated drinking water and increased cancer risks in humans (7).
Fluoride ion is not mutagenic in standard bacterial systems but has been associated with genetic aberrations in cultured human cells at doses much higher than expected for human exposure (6,8). Some in vivo studies report chromosomal aberrations in rodents while other studies using similar protocols report negative results (7).
Potential adverse reproductive effects of fluoride exposure in humans have not been adequately evaluated. Adverse reproductive effects of fluoride have been reported in animal studies, but at high concentrations sufficient to produce other manifestations of toxicity (9).

PREGNANCY

Pregnancy:Teratogenic Effects: Pregnancy Category B. Fluoride readily crosses the placenta (7,9). Animal studies (rats and rabbits) have shown that fluoride is not a teratogen (10,12,13). Maternal exposure to 18 mg Fluoride/kg of body weight did not affect maternal body weight, litter size or fetal weight and did not increase frequency of skeletal or visceral malformations (10). There are no adequate and well-controlled studies in pregnant women. Several epidemiological studies show no increase in birth defects in areas with fluoridated water compared to areas with low fluoridated water (7). However, caution should be exercised when fluoride is administered to pregnant women.

NURSING MOTHERS

Nursing Mothers: Due to the relative insensitivity of human milk fluoride levels to changes in maternal fluoride intake, and due to the low concentrations of fluoride in human milk, fluoride supplementation during lactation would not be expected to significantly affect fluoride intake by the nursing infant (11). However, caution should be exercised when fluoride is administered to nursing women.

PEDIATRIC USE

Pediatric Use: The use of fluoride solutions, gels, and foams containing up to 1.23 % fluoride ion as caries preventives in pediatric patients aged 6 to 16 years is supported by clinical studies in students aged 6 to 12 years (1,2). Safety and effectiveness in pediatric patients below the age of 6 years has not been established. Please refer to CONTRAINDICATIONS and WARNINGS sections.

GERIATRIC USE

Geriatric Use: No overall differences in safety or effectiveness have been observed between geriatric and younger patients. This drug is known to be substantially excreted by the kidney, therefore the risk of toxic reactions to this drug may be greater in patients with impaired renal function. Because elderly patients are more likely to have decreased renal function, care should be taken in dose selection, and it may be useful to monitor renal function.

ADVERSE REACTIONS

ADVERSE REACTIONS: Developing teeth of children under age 6 may become permanently discolored if excessive amounts are repeatedly swallowed. The following adverse reactions are possible in individuals hypersensitive to fluoride: eczema, atopic dermatitis, urticaria, gastric distress, headache and weakness.

OVERDOSAGE

OVERDOSAGE: Accidental ingestion of large amounts of fluoride can result in acute irritation of the mouth and gastrointestinal symptoms such as nausea, vomiting, diarrhea, hematemesis epigastric cramping and abdominal pain. If large amounts of fluoride equal to or greater than 5mg fluoride/kg body weight (or 2.3 mg fluoride/lb body weight) are ingested, give calcium (e.g. milk, 5% calcium gluconate or calcium lactate solution) orally to relieve gastrointestinal symptoms and admit immediately to a hospital facility.
A standard treatment dose of Minute-Foam contains approximately 12.4 mg fluoride. One 165 g (5.8oz) bottle contains approximately 1.95 g of fluoride.

DOSAGE AND ADMINISTRATION: Adults and Children 6 years and over: Use foam 2 times a year.
This initial time you dispense from a new bottle, gently lift upward on the nozzle to break the protective seal (thin plastic located adjacent to trigger). If this seal is broken do not use the product.
Shake bottle vigorously for 3-4 seconds prior to dispensing.
Invert bottle 180 degree with nozzle tip pointed downward into tray.
Place nozzle tip close to the tray floor and at one end of the tray arch. Moving from one end of the tray to the other in one fluid motion, slowly press down on the trigger.
Dispense foam into applicator tray. (Note: foam will expand slightly to fill the tray.)
Immediately place trays in mouth. (Do not fill trays with foam too far in advance of treatment as the foam will collapse and not be as effective.)
Have patient bite down on the trays lightly but firmly for 4 minutes.
Remove trays and have patient expectorate excess.
Instruct patient not to eat, drink, or rinse for at least 30 minutes.
For optimal tooth coverage, use a fluoride applicator tray which is deep enough to reach the entire vertical height of all teeth (even the molars)

HOW SUPPLIED

HOW SUPPLIED: Minute-Foam is available in a 165 g (5.8 oz) plastic aerosol container in six different flavors; NDC 0041-0340-06 Banana Splitz, NDC 0041-03141-06 Mellow Mint, NDC 0041-0342-06 Orang-a-Tangy, NDC 0041-0345-06 Bubblegum, NDC 0041-0346-06 Strawberry, NDC 0041-0347-06 Grape Punch.

REFERENCES:
(1.) Wellock, W.D. and Brudevold, F.: Arch. Oral Biol., 10, 453-460 (1965) (2.) Jiang, H et al.:J. Dent, 33, 469-473 (2005) (3.) National Toxicology Program: NTP TR 393, NIH Publication 91-2842, (1990) (4.) Bucker, J.R et al.L Int. J. Cancer 48, 1118-1126 (1990) (6.) Martin, G.R. et al.: Mutat. Res. 66, 159-167 (1979) (7.) Agency for toxic Substances and Disease Registry: Toxicological Profile for Fluorides (2003) (8.) Aardema, M.J. et al.: Mutat. Res. 331 (1), 171-172 (9.) National Research Council: Fluoride in Drinking Water (2006) (10.) Heindel, J.J. et al.: Fundam Appl Toxicol, 30, 162-177 (1996) (11.) Institute of Medicine, Food and Nutrition Board: Dietary Reference Intakes (1997) (12.) Collins, T.F et al.: Food Chem. Toxicol. 33 (11), 951-960 (13.) Collins, T.F. et al.: Food Chem Toxicol. 39 (8), 867-876

Minute Foam Label